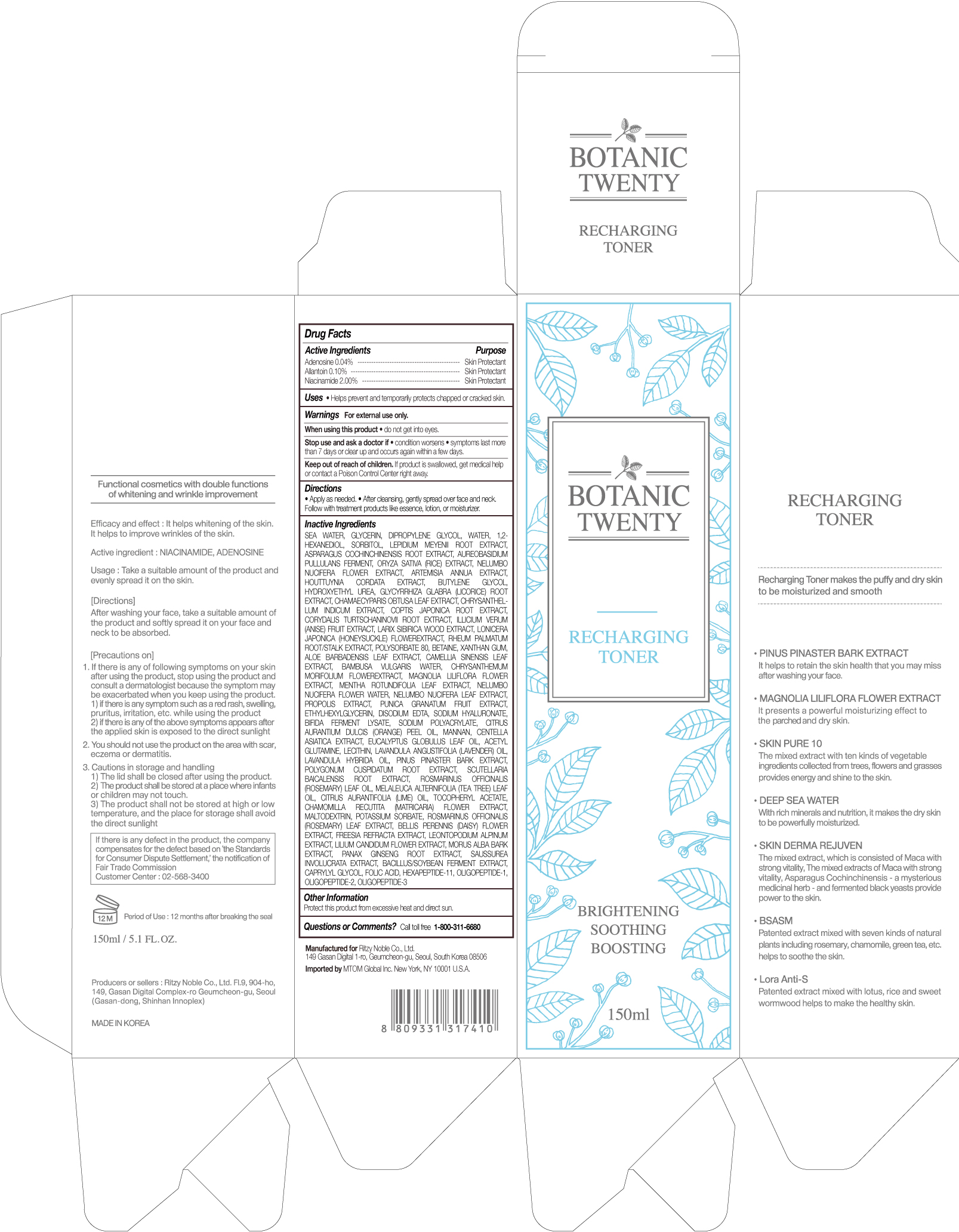 DRUG LABEL: BOTANIC TWENTY RECHARGING TONER
NDC: 71364-001 | Form: LIQUID
Manufacturer: RITZY NOBLE CO., LTD.
Category: otc | Type: HUMAN OTC DRUG LABEL
Date: 20180101

ACTIVE INGREDIENTS: ADENOSINE 0.04 g/150 mL; NIACINAMIDE 2 g/150 mL; ALLANTOIN 0.1 g/150 mL
INACTIVE INGREDIENTS: BETAINE; 1,2-HEXANEDIOL; DIPROPYLENE GLYCOL; NELUMBO NUCIFERA FLOWER; ARTEMISIA ANNUA WHOLE; SACCHAROMYCES LYSATE; BAMBUSA VULGARIS SAP; HYALURONIC ACID; BIFIDOBACTERIUM LONGUM; COPTIS JAPONICA ROOT; CHAMAECYPARIS OBTUSA LEAF; RHEUM PALMATUM ROOT; BUTYLENE GLYCOL; LEPIDIUM MEYENII ROOT; AUREOBASIDIUM PULLULANS VAR. PULLUTANS; WATER; GLYCERIN; LONICERA JAPONICA FLOWER; CHRYSANTHEMUM INDICUM FLOWER; CORYDALIS TURTSCHANINOVII WHOLE; ILLICIUM VERUM WHOLE; LARIX SIBIRICA WOOD; YEAST MANNAN; BEE PROPOLIS EXTRACT; ETHYLHEXYLGLYCERIN; CITRUS AURANTIUM FRUIT OIL; CENTELLA ASIATICA; EUCALYPTUS GLOBULUS LEAF; ACETYL GLUTAMIC ACID; LECITHIN, SOYBEAN; LAVANDULA ANGUSTIFOLIA FLOWER; LAVANDULA X INTERMEDIA FLOWER; PINUS PINASTER WOOD; POLYGONUM CUSPIDATUM ROOT; SCUTELLARIA BAICALENSIS ROOT; ROSMARINUS OFFICINALIS FLOWERING TOP OIL; MELALEUCA ALTERNIFOLIA LEAF; .ALPHA.-TOCOPHEROL ACETATE; MATRICARIA CHAMOMILLA FLOWERING TOP; MALTODEXTRIN; POTASSIUM SORBATE; ROSMARINUS OFFICINALIS WHOLE; BELLIS PERENNIS FLOWER; FREESIA ALBA FLOWER; LEONTOPODIUM ALPINUM; LILIUM CANDIDUM FLOWER; MORUS ALBA BARK; PANAX GINSENG ROOT WATER; CAMELLIA SINENSIS WHOLE; CHRYSANTHEMUM X MORIFOLIUM FLOWER; MAGNOLIA LILIIFLORA FLOWER; MENTHA X ROTUNDIFOLIA LEAF; NELUMBO NUCIFERA LEAF; PUNICA GRANATUM SEED; EDETATE DISODIUM; SODIUM POLYACRYLATE (2500000 MW); KONJAC MANNAN; SAUSSUREA INVOLUCRATA FLOWERING TOP; BACILLUS POLYFERMENTICUS; CAPRYLYL GLYCOL; FOLIC ACID; HEXAPEPTIDE-11; OLIGOPEPTIDE-10; ASPARAGUS COCHINCHINENSIS WHOLE; HYDROXYETHYL UREA; XANTHAN GUM; HOUTTUYNIA CORDATA TOP; ORYZA SATIVA WHOLE; SORBITOL; ALOE VERA LEAF; GLYCYRRHIZA GLABRA; POLYSORBATE 80

ACTIVE INGREDIENTS

ADENOSINE 0.04%

ALLANTOIN 0.10%

NIACINAMIDE 2.00%

PURPOSE

SKIN PROTECTANT

USES

Helps prevent and temporarily protects chapped or cracked skin.

WARNINGS

FOR EXTERNAL USE ONLY

WHEN USING THIS PRODUCT

• do not get into eyes.

STOP USE AND ASK A DOCTOR IF

• condition worsens

• symptoms last more than 7 days or clear up and occurs again within a few days.

KEEP OUT OF REACH OF CHILDREN

If product is swallowed, get medical help or contact a Poison Control Center right away.

DIRECTIONS

• Apply as needed.

• After cleansing, gently spread over face and neck. Follow with treatment products like essence, lotion, or moisturizer.

INACTIVE INGREDIENTS

SEA WATER, GLYCERIN, DIPROPYLENE GLYCOL, WATER, 1,2- HEXANEDIOL, SORBITOL, LEPIDIUM MEYENII ROOT EXTRACT, ASPARAGUS COCHINCHINENSIS ROOT EXTRACT, AUREOBASIDIUM PULLULANS FERMENT, ORYZA SATIVA (RICE) EXTRACT, NELUMBO NUCIFERA FLOWER EXTRACT, ARTEMISIA ANNUA EXTRACT, HOUTTUYNIA CORDATA EXTRACT, BUTYLENE GLYCOL, HYDROXYETHYL UREA, GLYCYRRHIZA GLABRA (LICORICE) ROOT EXTRACT, CHAMAECYPARIS OBTUSA LEAF EXTRACT, CHRYSANTHELLUM INDICUM EXTRACT, COPTIS JAPONICA ROOT EXTRACT, CORYDALIS TURTSCHANINOVII ROOT EXTRACT, ILLICIUM VERUM (ANISE) FRUIT EXTRACT, LARIX SIBIRICA WOOD EXTRACT, LONICERA JAPONICA (HONEYSUCKLE) FLOWEREXTRACT, RHEUM PALMATUM ROOT/STALK EXTRACT, POLYSORBATE 80, BETAINE, XANTHAN GUM, ALOE BARBADENSIS LEAF EXTRACT, CAMELLIA SINENSIS LEAF EXTRACT, BAMBUSA VULGARIS WATER, CHRYSANTHEMUM MORIFOLIUM FLOWEREXTRACT, MAGNOLIA LILIFLORA FLOWER EXTRACT, MENTHA ROTUNDIFOLIA LEAF EXTRACT, NELUMBO NUCIFERA FLOWER WATER, NELUMBO NUCIFERA LEAF EXTRACT, PROPOLIS EXTRACT, PUNICA GRANATUM FRUIT EXTRACT, ETHYLHEXYLGLYCERIN, DISODIUM EDTA, SODIUM HYALURONATE, BIFIDA FERMENT LYSATE, SODIUM POLYACRYLATE, CITRUS AURANTIUM DULCIS (ORANGE) PEEL OIL, MANNAN, CENTELLA ASIATICA EXTRACT, EUCALYPTUS GLOBULUS LEAF OIL, ACETYL GLUTAMINE, LECITHIN, LAVANDULA ANGUSTIFOLIA (LAVENDER) OIL, LAVANDULA HYBRIDA OIL, PINUS PINASTER BARK EXTRACT, POLYGONUM CUSPIDATUM ROOT EXTRACT, SCUTELLARIA BAICALENSIS ROOT EXTRACT, ROSMARINUS OFFICINALIS (ROSEMARY) LEAF OIL, MELALEUCA ALTERNIFOLIA (TEA TREE) LEAF OIL, CITRUS AURANTIFOLIA (LIME) OIL, TOCOPHERYL ACETATE, CHAMOMILLA RECUTITA (MATRICARIA) FLOWER EXTRACT, MALTODEXTRIN, POTASSIUM SORBATE, ROSMARINUS OFFICINALIS (ROSEMARY) LEAF EXTRACT, BELLIS PERENNIS (DAISY) FLOWER EXTRACT, FREESIA REFRACTA EXTRACT, LEONTOPODIUM ALPINUM EXTRACT, LILIUM CANDIDUM FLOWER EXTRACT, MORUS ALBA BARK EXTRACT, PANAX GINSENG ROOT EXTRACT, SAUSSUREA INVOLUCRATA EXTRACT, BACILLUS/SOYBEAN FERMENT EXTRACT, CAPRYLYL GLYCOL, FOLIC ACID, HEXAPEPTIDE-11, OLIGOPEPTIDE-1, OLIGOPEPTIDE-2, OLIGOPEPTIDE-3

OTHER INFORMATION

Protect this product from excessive heat and direct sun.

QUESTIONS OR COMMENTS?

Call toll free 1-800-311-6680